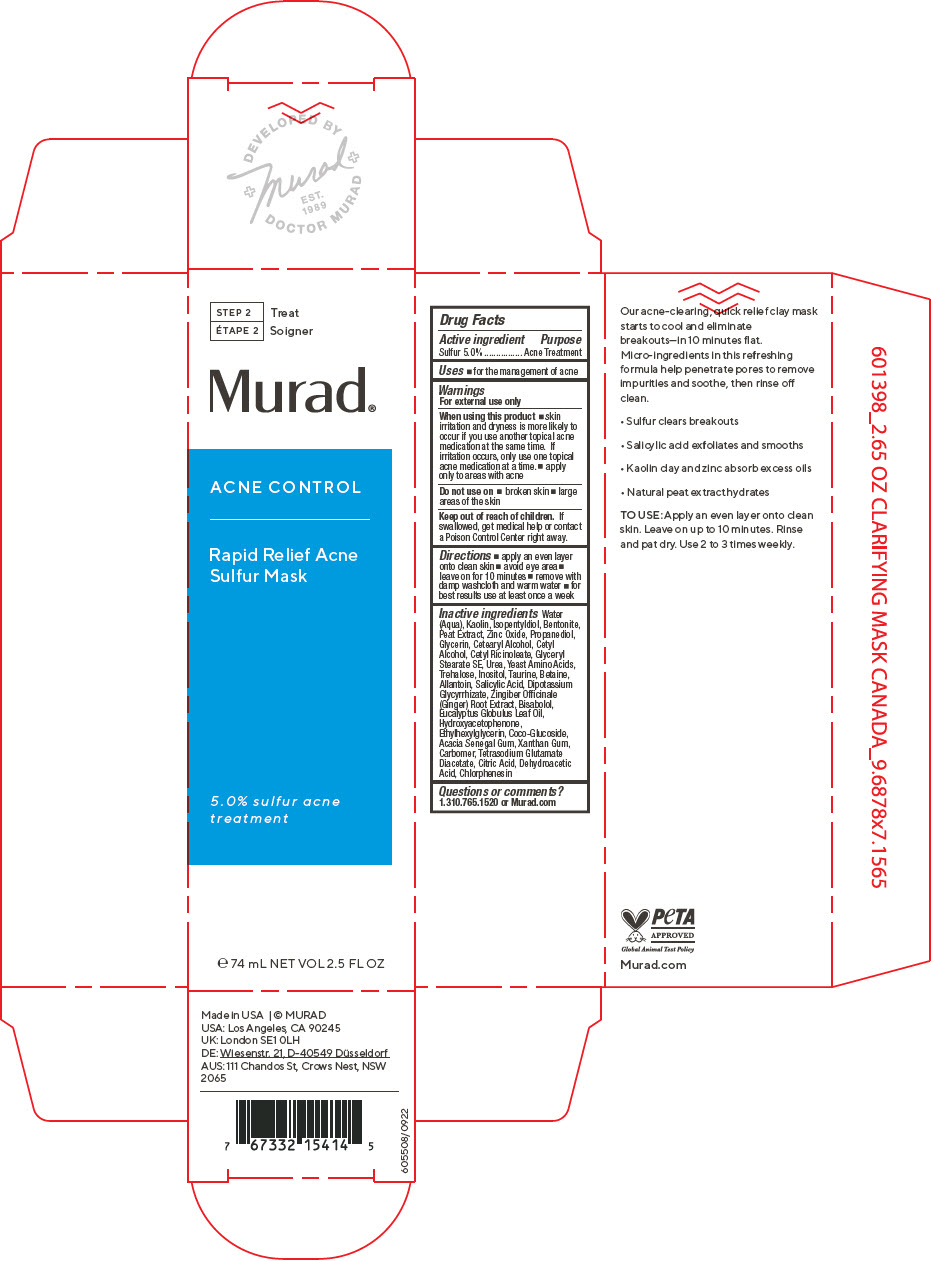 DRUG LABEL: Rapid Relief Acne Sulfur Mask
NDC: 70381-124 | Form: EMULSION
Manufacturer: Murad, LLC
Category: otc | Type: HUMAN OTC DRUG LABEL
Date: 20221026

ACTIVE INGREDIENTS: SULFUR 5 g/100 mL
INACTIVE INGREDIENTS: WATER; KAOLIN; ISOPENTYLDIOL; BENTONITE; ZINC OXIDE; PROPANEDIOL; GLYCERIN; CETOSTEARYL ALCOHOL; CETYL ALCOHOL; CETYL RICINOLEATE; GLYCERYL STEARATE SE; UREA; AMINO ACIDS, SOURCE UNSPECIFIED; TREHALOSE; INOSITOL; TAURINE; BETAINE; ALLANTOIN; SALICYLIC ACID; GLYCYRRHIZINATE DIPOTASSIUM; GINGER; LEVOMENOL; EUCALYPTUS OIL; HYDROXYACETOPHENONE; ETHYLHEXYLGLYCERIN; COCO GLUCOSIDE; ACACIA; XANTHAN GUM; CARBOMER HOMOPOLYMER, UNSPECIFIED TYPE; TETRASODIUM GLUTAMATE DIACETATE; CHLORPHENESIN; SPHAGNUM SQUARROSUM PEAT; CITRIC ACID MONOHYDRATE; DEHYDROACETIC ACID

Rapid Relief Acne Sulfur Mask

Drug Facts

Active ingredient

Sulfur 5.0%

Purpose

Acne Treatment

Uses

- for the management of acne

Warnings

For external use only

When using this product

- skin irritation and dryness is more likely to occur if you use another topical acne medication at the same time. If irritation occurs, only use one topical acne medication at a time.
- apply only to areas with acne

Do not use on

- broken skin
- large areas of the skin

Keep out of reach of children. If swallowed, get medical help or contact a Poison Control Center right away.

Directions

- apply an even layer onto clean skin
- avoid eye area
- leave on for 10 minutes
- remove with damp washcloth and warm water
- for best results use at least once a week

Inactive ingredients

Water (Aqua), Kaolin, Isopentyldiol, Bentonite, Peat Extract, Zinc Oxide, Propanediol, Glycerin, Cetearyl Alcohol, Cetyl Alcohol, Cetyl Ricinoleate, Glyceryl Stearate SE, Urea, Yeast Amino Acids, Trehalose, Inositol, Taurine, Betaine, Allantoin, Salicylic Acid, Dipotassium Glycyrrhizate, Zingiber Officinale (Ginger) Root Extract, Bisabolol, Eucalyptus Globulus Leaf Oil, Hydroxyacetophenone, Ethylhexylglycerin, Coco-Glucoside, Acacia Senegal Gum, Xanthan Gum, Carbomer, Tetrasodium Glutamate Diacetate, Citric Acid, Dehydroacetic Acid, Chlorphenesin

Questions or comments?

1.310.765.1520 or Murad.com

PRINCIPAL DISPLAY PANEL - 74 mL Tube Carton

STEP 2
Treat

Murad®

ACNE CONTROL

Rapid Relief Acne
Sulfur Mask

5.0% sulfur acne
treatment

℮ 74 mL NET VOL 2.5 FL OZ